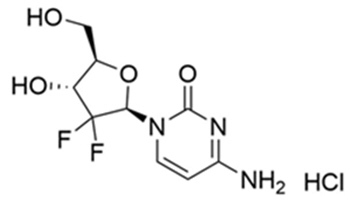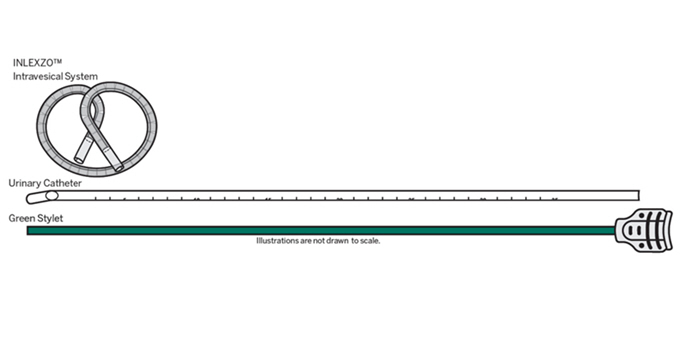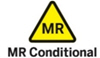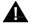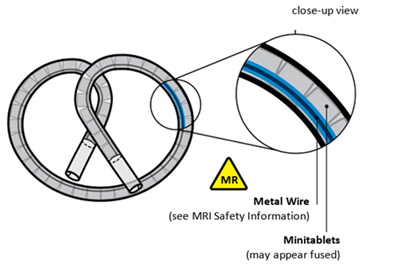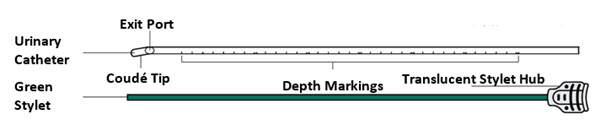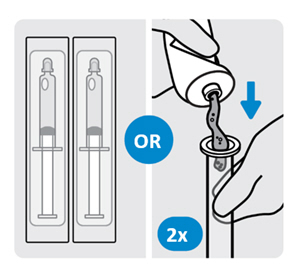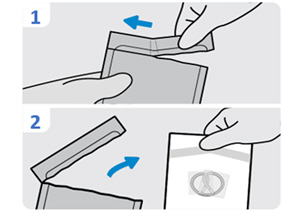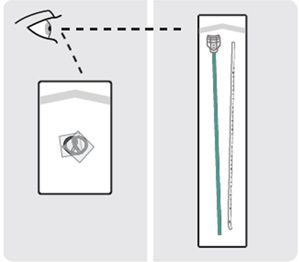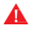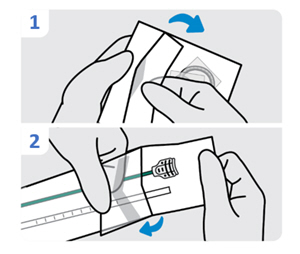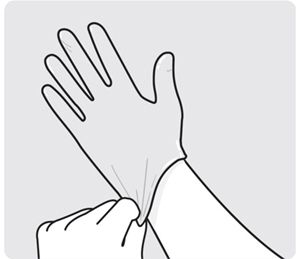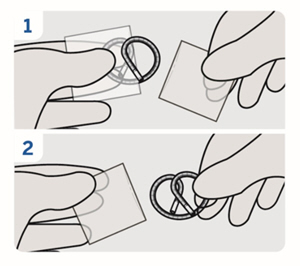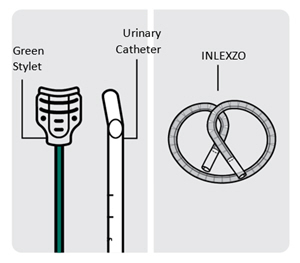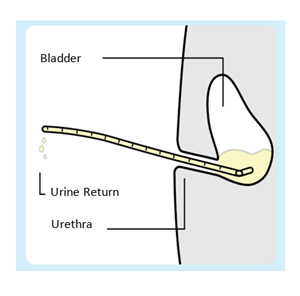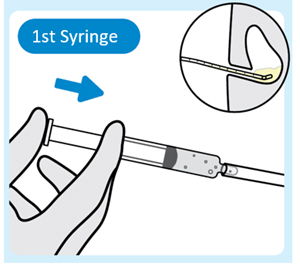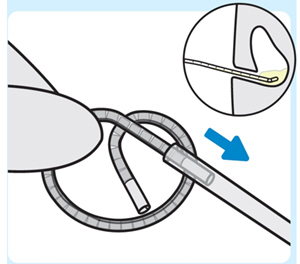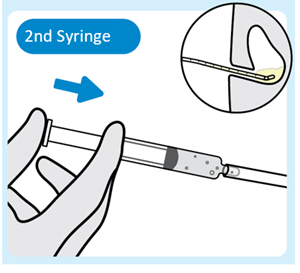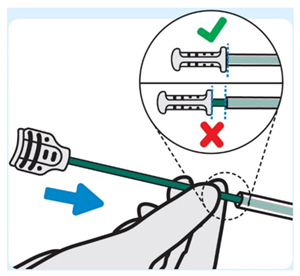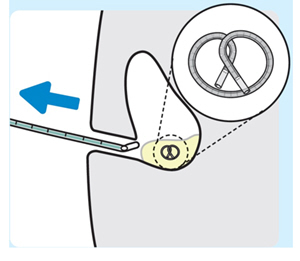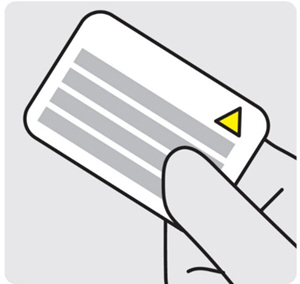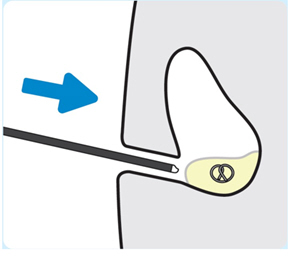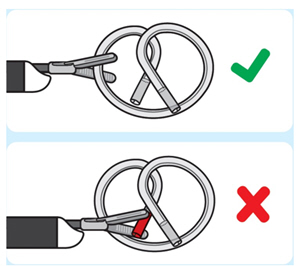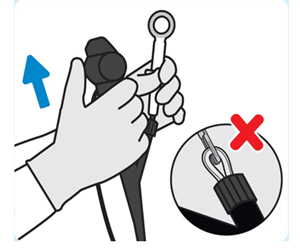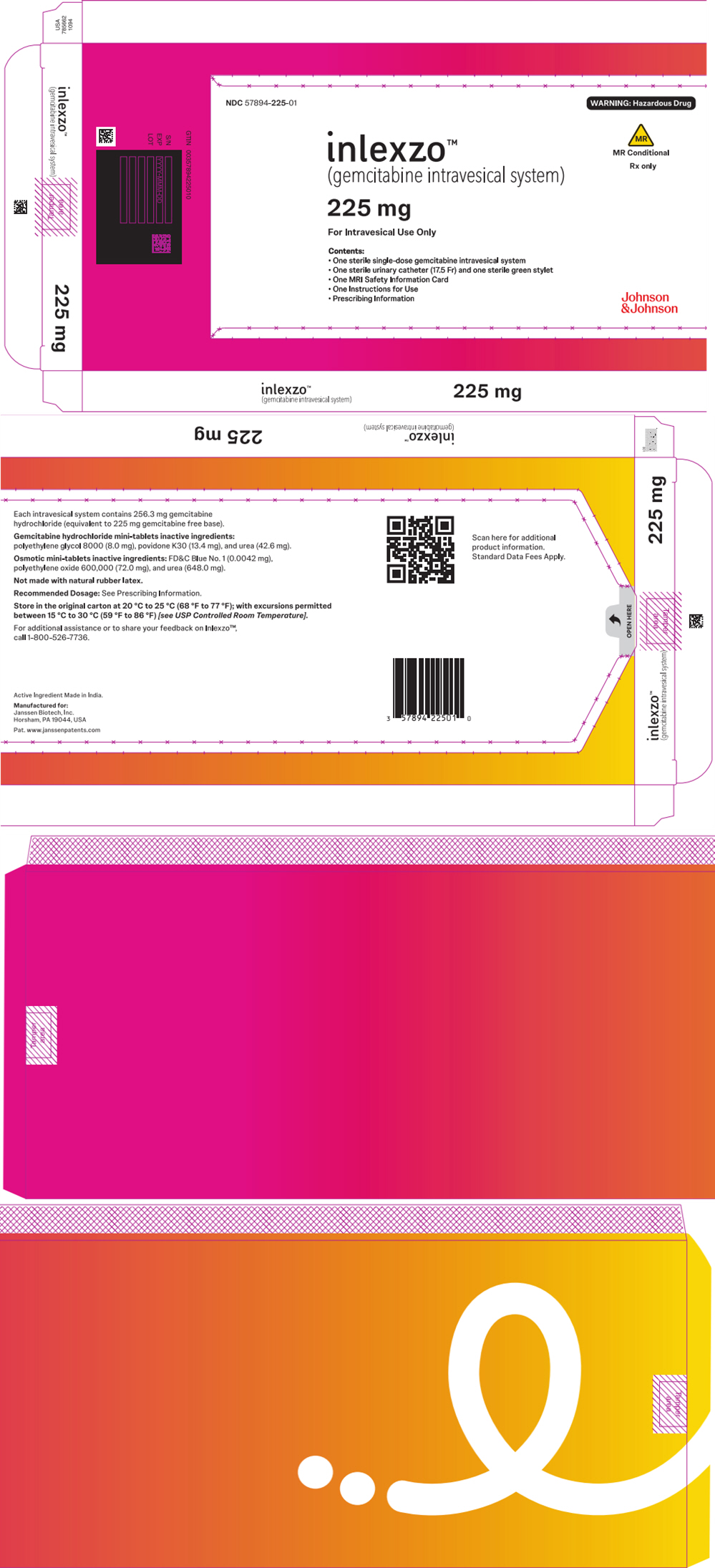 DRUG LABEL: INLEXZO
NDC: 57894-225 | Form: SYSTEM
Manufacturer: Janssen Biotech, Inc
Category: prescription | Type: HUMAN PRESCRIPTION DRUG LABEL
Date: 20250911

ACTIVE INGREDIENTS: GEMCITABINE 225 mg/1 1
INACTIVE INGREDIENTS: POLYETHYLENE GLYCOL 8000 8 mg/1 1; POVIDONE K30; UREA; FD&C BLUE NO. 1; POLYETHYLENE OXIDE 600000

HIGHLIGHTS OF PRESCRIBING INFORMATION

These highlights do not include all the information needed to use INLEXZO safely and effectively. See full prescribing information for INLEXZO.
INLEXZO™ (gemcitabine intravesical system)
Initial U.S. Approval: 2025

1 INDICATIONS AND USAGE

INLEXZO is a nucleoside metabolic inhibitor-containing intravesical system, indicated for the treatment of adult patients with Bacillus Calmette-Guérin (BCG)-unresponsive, non-muscle invasive bladder cancer (NMIBC) with carcinoma in situ(CIS) with or without papillary tumors. (1)

2 DOSAGE AND ADMINISTRATION

For Intravesical Administration Only

- Insert INLEXZO (225 mg of gemcitabine) into the bladder once every 3 weeks up to 6 months (8 doses), followed by once every 12 weeks (6 doses). (2.2)
- Insert into the bladder using the co-packaged urinary catheter and stylet only. (2.1)
- Remove INLEXZO after each 3-week indwelling period. (2.2)
- See Full Prescribing Information and Instructions for Use for insertion and removal procedures. (2.3)

3 DOSAGE FORMS AND STRENGTHS

- One single-dose 225 mg gemcitabine intravesical system (3)

4 CONTRAINDICATIONS

- Perforation of the bladder (4, 5.1)
- Prior hypersensitivity reaction to gemcitabine or any component of the product (4)

5 WARNINGS AND PRECAUTIONS

- Risks in Patients with Perforated Bladder: Evaluate the bladder before the intravesical insertion of INLEXZO. Do not administer to patients with a perforated bladder or in whom the integrity of the bladder mucosa has been compromised. (4, 5.1)
- Risk of Metastatic Bladder Cancer with Delayed Cystectomy: Delaying cystectomy can lead to the development of metastatic bladder cancer, which can be lethal. (5.2)
- Magnetic Resonance Imaging (MRI) Safety: INLEXZO can only be safely scanned with MRI under certain conditions. (5.3)
- Embryo-Fetal Toxicity: Can cause fetal harm. Advise patients of the potential risk to a fetus and to use effective contraception. (5.4, 8.1, 8.3)

6 ADVERSE REACTIONS

- The most common (>15%) adverse reactions, including laboratory abnormalities, are urinary frequency, urinary tract infection, dysuria, micturition urgency, decreased hemoglobin, increased lipase, urinary tract pain, decreased lymphocytes, hematuria, increased creatinine, increased potassium, increased AST, decreased sodium, bladder irritation, and increased ALT. (6.1)

To report SUSPECTED ADVERSE REACTIONS, contact Janssen Biotech, Inc. at 1-800-526-7736 (1-800-JANSSEN) or FDA at 1-800-FDA-1088 orwww.fda.gov/medwatch.

8 USE IN SPECIFIC POPULATIONS

- Lactation: Advise not to breastfeed. (8.2)

FULL PRESCRIBING INFORMATION

1 INDICATIONS AND USAGE

INLEXZO is indicated for the treatment of adult patients with Bacillus Calmette-Guérin (BCG)-unresponsive, non-muscle invasive bladder cancer (NMIBC) with carcinoma in situ(CIS), with or without papillary tumors.

2 DOSAGE AND ADMINISTRATION

2.1 Important Administration Instructions

Administer INLEXZO intravesically only. Do NOT administer by any other route. INLEXZO is co-packaged with a urinary catheter and stylet used to insert INLEXZO through the urinary catheter into the bladder. Administer using the co-packaged urinary catheter and stylet only.

INLEXZO should be inserted and removed by a trained healthcare provider. Healthcare providers should become thoroughly familiar with the insertion and removal instructions before attempting insertion or removal of INLEXZO.

Prophylactic antibiotics may be used at the discretion of the treating healthcare provider with each INLEXZO insertion and removal.

2.2 Recommended Dosage

Insert INLEXZO (225 mg of gemcitabine) into the bladder once every 3 weeks for up to 6 months (8 doses), followed by once every 12 weeks for up to 18 months (6 doses), or until persistent or recurrent NMIBC, disease progression, or unacceptable toxicity.

Remove INLEXZO after each 3-week indwelling period.

Missed Dose

If a dose is missed, it should be administered as closely as possible to the original treatment schedule.

2.3 Preparation and Intravesical Administration

See the Instructions for Useenclosed in the carton for complete information on preparation, intravesical administration, and removal of INLEXZO.

INLEXZO is a hazardous drug. Follow applicable special handling and disposal procedures while handling INLEXZO and during the insertion and removal procedure.^1

Instruct patients to drink approximately 1500 mL of fluids per day during therapy with INLEXZO to ensure adequate urine production for drug release.

Instruct patients not to empty the bladder immediately prior to the insertion procedure. Presence of urine in the bladder can facilitate deployment of INLEXZO. Patients can resume micturition after the insertion procedure.

During indwelling period of approximately 3 weeks, advise patients to avoid urine contact with skin, to void urine sitting on a toilet, to wash hands with soap and water and to wash their genital area with water after each urination, and to flush the toilet after use.

3 DOSAGE FORMS AND STRENGTHS

One single-dose 225 mg strength gemcitabine intravesical system consisting of a flexible bi-oval shaped tube containing an almost white to light pink-brown colored component at the center surrounded by off white to light blue components.

4 CONTRAINDICATIONS

INLEXZO is contraindicated in patients with:

- Perforation of the bladder [see Warnings and Precautions (5.1)] .
- Prior hypersensitivity reactions to gemcitabine or any component of the product.

5 WARNINGS AND PRECAUTIONS

5.1 Risks in Patients with Perforated Bladder

INLEXZO may lead to systemic exposure to gemcitabine and to severe adverse reactions if administered to patients with a perforated bladder or to those in whom the integrity of the bladder mucosa has been compromised.

Evaluate the bladder before the intravesical administration of INLEXZO and do not administer to patients with a perforated bladder or mucosal compromise until bladder integrity has been restored [see Contraindications (4)].

5.2 Risk of Metastatic Bladder Cancer with Delayed Cystectomy

Delaying cystectomy in patients with BCG-unresponsive CIS could lead to development of muscle invasive or metastatic bladder cancer, which can be lethal. The risk of developing muscle invasive or metastatic bladder cancer increases the longer cystectomy is delayed in the presence of persisting CIS.

Of the 83 evaluable patients with BCG-unresponsive CIS treated with INLEXZO in Cohort 2 of SunRISe-1, seven patients (8%) progressed to muscle invasive (T2 or greater) bladder cancer. Three patients (3.5%) had progression determined at the time of cystectomy. The median time between determination of persistent or recurrent CIS or T1 and progression to muscle invasive disease was 94 days.

5.3 Magnetic Resonance Imaging (MRI) Safety

INLEXZO may be used with MRI only under the specific predefined conditions provided below to avoid potential safety hazards or severe adverse reactions.

Based on clinical experience in patients treated with INLEXZO indwelling in the bladder who underwent MRI scans and nonclinical testing, INLEXZO is MR Conditional. A patient with INLEXZO indwelling in the bladder can be scanned in an MR system under the following conditions:

- Static magnetic field of 1.5-Tesla and 3-Tesla, only.
- Maximum spatial gradient magnetic field of 5000 Gauss/cm or less.
- Maximum magnetic resonance system reported, whole body averaged specific absorption rate of 2-W/kg for 60 minutes of continuous scanning (i.e., per pulse sequence or back-to-back sequences without breaks) in the Normal Operating Mode of operation for the MR system.

Under the scan conditions defined, INLEXZO is expected to produce a maximum temperature rise of 2°C after 15 minutes of continuous scanning.

In nonclinical testing, the image artifact caused by INLEXZO extends approximately 2 mm from INLEXZO using a gradient echo pulse sequence and a 3-Tesla MR system.

5.4 Embryo-Fetal Toxicity

Based on animal data and its mechanism of action, INLEXZO can cause fetal harm when administered to a pregnant woman if systemic exposure occurs [see Clinical Pharmacology (12.1)] . In animal reproduction studies, systemic administration of gemcitabine was teratogenic, embryotoxic, and fetotoxic in mice and rabbits.

Advise pregnant women and females of reproductive potential of the potential risk to a fetus. Advise females of reproductive potential to use effective contraception during treatment and for 6 months after final removal of INLEXZO. Advise male patients with female partners of reproductive potential to use effective contraception during treatment and for 3 months after final removal of INLEXZO [see Use in Specific Populations (8.1, 8.3)] .

6 ADVERSE REACTIONS

6.1 Clinical Trials Experience

Because clinical trials are conducted under widely varying conditions, adverse reaction rates observed in the clinical trials of a drug cannot be directly compared to rates in the clinical trials of another drug and may not reflect the rates observed in practice.

The safety of INLEXZO monotherapy was evaluated in Cohort 2 of SunRISe-1, a multi-center, open-label study in 85 adult patients with BCG-unresponsive NMIBC with CIS, with or without papillary tumors [see Clinical Studies (14.1)].

Patients received INLEXZO (225 mg of gemcitabine) inserted into the bladder every 3 weeks for 6 months, followed by once every 12 weeks for up to 18 months, or until unacceptable toxicity, disease persistence, recurrence, or progression [see Dosage and Administration (2.2)] .

The median number of doses of INLEXZO administered to patients was 9 (range: 1 to 14) doses. The median duration of exposure to INLEXZO was 41 weeks (range: 1 to 108 weeks).

Serious adverse reactions occurred in 24% of patients receiving INLEXZO. Serious adverse reactions that occurred in >2% of patients included urinary tract infection, hematuria, pneumonia, and urinary tract pain. Fatal adverse reactions occurred in 1.2% of patients who received INLEXZO, including cognitive disorder.

Permanent discontinuation of INLEXZO due to an adverse reaction occurred in 7% of patients. Adverse reactions which resulted in permanent discontinuation of INLEXZO in >1% of patients included bladder irritation, urinary frequency, cognitive disorder, hydronephrosis, and urinary tract disorder.

Dosage interruptions of INLEXZO due to an adverse reaction occurred in 41% of patients. Adverse reactions which required dosage interruption in >3% of patients included urinary tract infection, urinary tract pain, hematuria, urinary frequency, micturition urgency, dysuria, and genital pain.

The most common (>15%) adverse reactions, including laboratory abnormalities, were urinary frequency, urinary tract infection, dysuria, micturition urgency, decreased hemoglobin, increased lipase, urinary tract pain, decreased lymphocytes, hematuria, increased creatinine, increased potassium, increased AST, decreased sodium, bladder irritation, and increased ALT.

Table 1 summarizes the adverse reactions in SunRISe-1.

Table 1: Adverse Reactions Occurring in >15% of Patients in SunRISe-1
Adverse Reaction | INLEXZO N=85
Adverse Reaction | All Grades % | Grade 3 or 4 %
Urinary frequency | 48 | 0
Urinary tract infection [Includes other related terms] | 44 | 6
Dysuria | 42 | 0
Micturition urgency | 34 | 0
Urinary tract pain | 26 | 7
Hematuria | 24 | 2.4
Bladder irritation | 16 | 0

Other clinically significant adverse reactions (<15%) included fatigue (14%), genital pain (12%), diarrhea (11%), urinary incontinence (9%), urinary retention (7%), and nocturia (4.7%).

Table 2: Select Laboratory Abnormalities (>15%) That Worsened from Baseline in Patients Who Received INLEXZO in SunRISe-1
Laboratory Abnormality | INLEXZO [The denominator used to calculate the rate varied from 82 to 83 based on the number of patients with a baseline value and at least one post-treatment value.]
Laboratory Abnormality | All Grades (%) | Grade 3 or 4 (%)
Hematology
Decreased Hemoglobin | 31 | 1.2
Decreased Lymphocytes | 24 | 4.8
Chemistry
Increased Lipase | 28 | 12
Increased Creatinine | 24 | 0
Increased Potassium | 22 | 1.2
Increased AST | 17 | 1.2
Decreased Sodium | 16 | 4.8
Increased ALT | 16 | 1.2

8 USE IN SPECIFIC POPULATIONS

8.1 Pregnancy

Risk Summary

Based on animal data and its mechanism of action, INLEXZO can cause fetal harm when administered to a pregnant woman if systemic exposure occurs [see Clinical Pharmacology (12.1)] . There are no available data on the use of INLEXZO in pregnant women to inform a drug-associated risk. In animal reproduction studies, systemic administration of gemcitabine was teratogenic, embryotoxic, and fetotoxic in mice and rabbits (see Data) . Advise pregnant women and females of reproductive potential of the potential risk to a fetus.

In the U.S. general population, the estimated background risk of major birth defects and miscarriages in clinically recognized pregnancies is 2 to 4% and 15 to 20%, respectively.

Data

Animal Data

Gemcitabine is embryotoxic in mice. Daily systemic dosing of gemcitabine to pregnant mice increased the incidence of fetal malformation (cleft palate, incomplete ossification) at doses of 1.5 mg/kg/day. Gemcitabine was embryotoxic and fetotoxic in rabbits. Daily systemic dosing of gemcitabine to pregnant rabbits resulted in fetotoxicity (decreased fetal viability, reduced litter sizes, and developmental delays) and increased the incidence of fetal malformations (fused pulmonary artery, absence of gall bladder) at doses of 0.1 mg/kg/day.

8.2 Lactation

Risk Summary

There is no information regarding the presence of gemcitabine or its metabolites in human milk, or their effects on the breastfed infant or milk production following INLEXZO administration. Because of the potential for serious adverse reactions in breastfed infants, advise women not to breastfeed during treatment and for 1 week after final removal of INLEXZO.

8.3 Females and Males of Reproductive Potential

INLEXZO can cause fetal harm when administered to a pregnant woman [see Use in Specific Populations (8.1)].

Pregnancy Testing

Verify pregnancy status in females of reproductive potential prior to initiating INLEXZO.

Contraception

Females

Advise females of reproductive potential to use effective contraception during treatment and for 6 months after final removal of INLEXZO.

Males

Because of the potential for genotoxicity, advise males with female partners of reproductive potential to use effective contraception during treatment and for 3 months after final removal of INLEXZO [see Nonclinical Toxicology (13.1)] .

Infertility

Males

Based on animal studies, INLEXZO may impair fertility in males of reproductive potential [see Nonclinical Toxicology (13.1)] . It is not known whether these effects on fertility are reversible.

8.4 Pediatric Use

Safety and effectiveness of INLEXZO in pediatric patients have not been established.

8.5 Geriatric Use

Of the patients given INLEXZO monotherapy in Cohort 2 of SunRISe-1, 72% were 65 years of age or older and 34% were 75 years or older. There were insufficient numbers of patients <65 years of age to determine if these patients respond differently to patients 65 years of age and older.

11 DESCRIPTION

INLEXZO contains gemcitabine hydrochloride, a nucleoside metabolic inhibitor. Gemcitabine hydrochloride is 2'-deoxy-2',2'- difluorocytidine monohydrochloride (β-isomer) with a molecular formula of C9H11F2N3O4 ∙ HCl, and a molecular weight of 299.66. The structural formula is:

INLEXZO is a sterile, non-resorbable intravesical system containing the equivalent of 225 mg gemcitabine (present as 256.3 mg of gemcitabine hydrochloride).

Gemcitabine Intravesical System

INLEXZO is a bi-oval-shaped tube containing an almost white to light pink-brown colored gemcitabine component at the center surrounded on each side by off white to light blue-colored osmotic components.

- The gemcitabine component contains 225 mg of gemcitabine and the following inactive ingredients: polyethylene glycol 8000 (8.0 mg), povidone K30 (13.4 mg), and urea (42.6 mg).
- The osmotic components contain the following inactive ingredients: FD&C Blue No.1 (0.0042 mg), polyethylene oxide 600,000 (72.0 mg), and urea (648.0 mg).

The silicone tube contains two lumens, the larger one containing the drug components and silicone spacers, and the smaller one containing a superelastic nitinol wire in a predefined shape (wireform). Both lumens are capped with a silicone adhesive. The lumen containing the gemcitabine and osmotic components has a single delivery orifice. INLEXZO's coiled dimensions are approximately 5.5 cm wide × 4.5 cm high.

Urinary Catheter and Stylet

INLEXZO is co-packaged with a sterile urinary catheter and a sterile stylet, required for transurethral insertion into the bladder. The urinary catheter and stylet are made of thermoplastic elastomer and polyethene, and consist of the following components:

- A semi-transparent urinary catheter, with a rounded blunt distal tip that includes a coudé tip, a product exit port near the distal tip, and a lumen which extends from the exit port to an open proximal end. The outer diameter of the urinary catheter is 5.82 mm (17.5 Fr). Printed depth markings are placed on the urinary catheter to indicate insertion depth and orientation of the coudé tip to assist the user during insertion.
- A green stylet with a hub at the proximal end is used to advance INLEXZO through the urinary catheter lumen and into the bladder. The stylet length and proximal hub prevent the stylet's distal end from advancement beyond the exit port.

12 CLINICAL PHARMACOLOGY

12.1 Mechanism of Action

Gemcitabine kills cells undergoing DNA synthesis and blocks the progression of cells through the G1/S-phase boundary. Gemcitabine is metabolized by nucleoside kinases to diphosphate (dFdCDP) and triphosphate (dFdCTP) nucleosides. Gemcitabine diphosphate inhibits ribonucleotide reductase, an enzyme responsible for catalyzing the reactions that generate deoxynucleoside triphosphates for DNA synthesis, resulting in reductions in deoxynucleotide concentrations, including dCTP. Gemcitabine triphosphate competes with dCTP for incorporation into DNA. The reduction in the intracellular concentration of dCTP by the action of the diphosphate enhances the incorporation of gemcitabine triphosphate into DNA (self-potentiation). After the gemcitabine nucleotide is incorporated into DNA, only one additional nucleotide is added to the growing DNA strands, which eventually results in the initiation of apoptotic cell death.

12.2 Pharmacodynamics

The exposure-response relationship and time-course of pharmacodynamic response for the safety and effectiveness of INLEXZO have not been fully characterized.

12.3 Pharmacokinetics

The systemic exposure of gemcitabine and the inactive uracil metabolite (2´-deoxy-2´,2´-difluorouridine [dFdU]), were evaluated between Days 2 and 7 during the indwelling period. The plasma gemcitabine concentrations were below the lower limit of quantification (0.1 µg/mL) in all patients at all time points. Eighteen patients (17%) had at least one quantifiable plasma dFdU concentration above the lower limit of quantification (0.1 µg/mL) and the maximum observed plasma dFdU concentration was 0.4 µg/mL. Plasma concentrations of both gemcitabine and dFdU are estimated to be less than 1% of the expected Cmaxafter intravenous administration of gemcitabine.

Excretion

Gemcitabine and dFdU are excreted in urine throughout the indwelling period for INLEXZO. Of the total gemcitabine dose, 77% was excreted by Day 7 and 99% was excreted by Day 21 in urine as gemcitabine and dFdU.

Mean urinary excretion on Days 2 through 5 ranged from 21 to 32 mg per day excreted in the urine as gemcitabine and dFdU.

13 NONCLINICAL TOXICOLOGY

13.1 Carcinogenesis, Mutagenesis, Impairment of Fertility

Long-term animal studies to evaluate the carcinogenic potential of gemcitabine have not been conducted. Gemcitabine was mutagenic in an in vitromouse lymphoma (L5178Y) assay and was clastogenic in an in vivomouse micronucleus assay.

Dedicated animal fertility studies have not been conducted with gemcitabine intravesical system. Gemcitabine intraperitoneal doses of 0.5 mg/kg/day in male mice resulted in moderate to severe hypospermatogenesis, decreased fertility, and decreased implantations. In female mice, fertility was not affected but maternal toxicities were observed at 1.5 mg/kg/day administered intravenously and fetotoxicity or embryo lethality were observed at 0.25 mg/kg/day administered intravenously.

14 CLINICAL STUDIES

14.1 BCG-unresponsive NMIBC

The efficacy of INLEXZO was evaluated in Cohort 2 of SunRISe-1 (NCT04640623), a single-arm, multi-center trial in 83 adults with BCG-unresponsive, NMIBC with CIS, with or without papillary tumors (T1, or high-grade Ta) following transurethral resection.

BCG-unresponsive NMIBC CIS was defined as persistent or recurrent CIS alone or with Ta/T1 disease within 12 months of adequate BCG therapy. Adequate BCG therapy was defined as a minimum administration of at least five of six doses of an initial induction course plus either of: at least two of three doses of maintenance therapy or at least two of six doses of a second induction course. Prior to treatment, all patients had undergone transurethral resection of bladder tumor (TURBT) to remove all resectable disease (Ta and T1 components). Residual CIS (Tis components) not amenable to complete resection was permitted. The trial included patients who were ineligible for or who had elected not to undergo radical cystectomy and excluded patients with extra-vesical (i.e., urethra, ureter, or renal pelvis), muscle invasive (T2-T4), locally advanced, or metastatic urothelial carcinoma.

Patients received INLEXZO (225 mg of gemcitabine) into the bladder every 3 weeks for 6 months, followed by once every 12 weeks for up to 18 months, or until unacceptable toxicity, persistence or recurrence of CIS and/or high-grade papillary disease, or progression [see Dosage and Administration (2.2)]. Tumor status was assessed every 12 weeks during the initial two years of treatment, after which cystoscopy was performed at least every 24 weeks. Mandatory biopsies were performed 24 and 48 weeks after treatment initiation.

The major efficacy outcome measures were complete response rate at any time (defined as negative results for cystoscopy [with TURBT and centrally-reviewed biopsies as applicable] and centrally-reviewed urine cytology) and duration of response.

The median age of patients was 71 years (range: 40 to 88); 80% male; 87% White, 10% Asian, 2.4% Black or African American and 1.2% race not reported; 10% were of Hispanic or Latino ethnicity, 89% identified as not Hispanic or Latino, and 1.2% were ethnicity unknown or not reported. Baseline ECOG performance status was 0 (92%) or 1 (8%). Tumor pattern at study entry was CIS only (67%), CIS with high-grade Ta only (22%), and CIS with T1 (11%). All patients had predominant urothelial carcinoma including 1 patient (1.2%) with squamous differentiation. The median number of prior instillations of BCG was 12 (range: 7 to 42).

Efficacy results are summarized in Table 3.

Table 3: Efficacy Results in SunRISe-1
Endpoint | INLEXZO N=83
Complete Response Rate (95% CI) | 82% (72, 90)
Duration of Response [Based on patients (n=68) with a complete response at any time; reflects period from the time complete response was achieved.]
Range in months | 0+, 44+
% (n) with duration ≥12 months | 51% (35)
CI= confidence interval.
+ Denotes ongoing response

15 REFERENCES

1. OSHA Hazardous Drugs. Occupational Safety and Health Administration. Available at: https://www.osha.gov/hazardous-drugs (Accessed: 06 September 2024).

16 HOW SUPPLIED/STORAGE AND HANDLING

How Supplied

INLEXZO (gemcitabine intravesical system) contains 225 mg gemcitabine.

INLEXZO (NDC# 57894-225-01) is available in a carton containing:

- One sterile single-dose of INLEXZO in two clear laminate sleeves and packaged in an inner pouch. The inner pouch and a desiccant are packaged in an outer foil pouch. The outside surfaces of the inner and outer pouches are not sterile.
- One sterile urinary catheter and one sterile stylet packaged together in a pouch.

Storage

Store in the original carton at 20°C to 25°C (68°F to 77°F); with excursions permitted between 15°C to 30°C (59°F to 86°F) [see USP Controlled Room Temperature].

Handling

INLEXZO is a hazardous drug. Follow applicable special handling and disposal procedures.^1

17 PATIENT COUNSELING INFORMATION

Advise patients to read the FDA-approved patient labeling (Patient Information).

Risk of Metastatic Bladder Cancer with Delayed Cystectomy

- Inform patients that delaying cystectomy could lead to development of metastatic bladder cancer. Discuss the risk of metastatic bladder cancer and that the risk increases the longer cystectomy is delayed in the presence of persistent CIS [see Warnings and Precautions (5.2)] .

Magnetic Resonance Imaging (MRI) Safety

- Inform patients that INLEXZO can only be safely scanned with MRI under specific conditions [see Warnings and Precautions (5.3)] . Instruct patients who will have an MRI to tell their healthcare provider that they have INLEXZO.
- This information is included in the MRI Safety Information Card. Complete the MRI Safety Information Card and give it to the patient.

Embryo-Fetal Toxicity

- Advise females of reproductive potential of the potential risk to a fetus and to inform their healthcare provider of a known or suspected pregnancy [see Warnings and Precautions (5.4)and Use in Specific Populations (8.1)].
- Advise females of reproductive potential to use effective contraception during treatment and for 6 months after final removal of INLEXZO [see Use in Specific Populations (8.3)] .
- Advise males with female partners of reproductive potential to use effective contraception during treatment and for 3 months after final removal of INLEXZO [see Use in Specific Populations (8.3)].

Lactation

- Advise women not to breastfeed during treatment and for 1 week after final removal of INLEXZO [see Use in Specific Populations (8.2)].

Infertility

- Advise males of reproductive potential that INLEXZO may impair fertility [see Use in Specific Populations (8.3)] .

Important Post-Treatment Instructions

- Instruct patients not to empty the bladder immediately prior to the insertion procedure.
- Advise patients to avoid contact with urine while INLEXZO is indwelling in the bladder and for at least 24 hours post-removal [see Clinical Pharmacology (12.3)] .
- Advise patients to avoid urine contact with skin by voiding sitting on a toilet, flushing the toilet after use, and to wash hands with soap and water and to wash their genital area with water after each urination.
- Advise patients to wash clothing soiled with urine promptly and separately from other clothing [see Dosage and Administration (2.3)].

Manufactured for:
Janssen Biotech, Inc.
Horsham, PA 19044, USA
U.S. License Number 1864

For patent information: www.janssenpatents.com

© Johnson & Johnson and its affiliates 2025

PATIENT INFORMATION
INLEXZO™ (inn-lex-zo)
(gemcitabine intravesical system)

What is INLEXZO?

- INLEXZO is a prescription medicine for the treatment of adults with a type of cancer of the lining of the bladder called non-muscle invasive bladder cancer (NMIBC), that has not spread to other parts of the body, and that did not respond to treatment with Bacillus Calmette-Guérin (BCG).

It is not known if INLEXZO is safe and effective for use in children.

Do not receive INLEXZO if you:

- have a tear or hole (perforation) of your bladder.
- have had an allergic reaction to gemcitabine or any of the ingredients in INLEXZO. See the end of this Patient Information leaflet for a complete list of ingredients in INLEXZO.

Before receiving INLEXZO, tell your healthcare provider about all of your medical conditions, including if you:

- are pregnant, or plan to become pregnant. INLEXZO can harm your unborn baby. You should not become pregnant during treatment with INLEXZO. Tell your healthcare provider right away if you become pregnant or think you may be pregnant during treatment with INLEXZO.
  Females who are able to become pregnant:
  - Your healthcare provider will check to see if you are pregnant before starting treatment with INLEXZO.
  - Use effective birth control (contraception) during treatment with INLEXZO and for 6 months after final removal of INLEXZO.
  Males treated with INLEXZO:
  - If you have a female partner who is able to become pregnant, you should use effective birth control (contraception) during treatment with INLEXZO and for 3 months after final removal of INLEXZO.
- are breastfeeding, or plan to breastfeed. It is not known if INLEXZO passes into your breastmilk. Do not breastfeed during treatment with INLEXZO and for 1 week after final removal of INLEXZO.

Tell your healthcare provider about all the medicines you take,including prescription and over-the-counter medicines, vitamins, and herbal supplements.

How will I receive INLEXZO?

- INLEXZO will be inserted and removed by your healthcare provider.
- INLEXZO is inserted into your bladder through a tube called a urinary catheter 1 time every 3 weeks for up to 6 months (8 doses) and then 1 time every 12 weeks for up to 18 months (6 doses).
- INLEXZO is removed after 3 weeks of being inserted (3-week indwelling period).
- Your healthcare provider will decide how many INLEXZO treatments you will receive.
- Your healthcare provider may give you antibiotics before INLEXZO is inserted or removed.
- It is very important that you go to all of your appointments. If you miss any appointments, call your healthcare provider as soon as possible to schedule your appointment.

Before receiving INLEXZO:

- Do not empty your bladder right before your procedure to insert INLEXZO.

After receiving INLEXZO:

- Drink about 6 to 7 cups (1500 mL) of fluids per day during treatment with INLEXZO to make sure you produce enough urine for the medicine to be released into the bladder.
- You can urinate normally. There is no need to hold your urine.
- Avoid contact between your skin and urine.
- To urinate, males and femalesshould sit on the toilet and flush after each use.
- Wash your hands with soap and water and wash your genital area with water after each time you urinate.
- Wash clothing soiled with urine right away and separately from other clothing.

After your healthcare provider removes INLEXZO:

- Avoid contact between your skin and urine for at least 24 hours after INLEXZO is removed.

What should I avoid after INLEXZO is inserted?
Tell your healthcare provider that you have INLEXZO before having a type of scan called Magnetic Resonance Imaging (MRI).

INLEXZO may be used under specific conditions.Your healthcare provider will give you an MRI Safety Information Card. Keep the card in a safe place and show it to all of your healthcare providers. The card contains important information in case you need to have an MRI. Your healthcare provider will review the information on the MRI Safety Information Card and determine the conditions they can safely do an MRI scan while INLEXZO is in your bladder.

What are the possible side effects of INLEXZO?
The most common side effects of INLEXZO include:

- frequent need to pass urine more often than usual
- urinary tract infection
- pain or burning sensation when passing urine
- urgent need to pass urine
- decreased hemoglobin
- increased lipase
- pain in the urinary tract (felt in the lower stomach area or lower back)

- decreased lymphocytes
- blood in urine
- increased creatinine
- increased potassium
- increased aspartate aminotransferase
- decreased sodium
- bladder irritation
- increased alanine transaminase

INLEXZO may cause fertility problems in males, which may affect your ability to have children. It is unknown if these side effects of fertility are reversible. Talk to your healthcare provider if this is a problem for you.
Tell your healthcare provider if you have any side effect that bothers you or does not go away.
These are not all the possible side effects of INLEXZO.
Call your healthcare provider for medical advice about side effects. You may report side effects to FDA at 1-800-FDA-1088.

General information about the safe and effective use of INLEXZO.
Medicines are sometimes prescribed for purposes other than those listed in this Patient Information leaflet. You can ask your pharmacist or healthcare provider for information about INLEXZO that is written for healthcare professionals.

What are the ingredients in INLEXZO?
Active ingredient:gemcitabine hydrochloride
Inactive ingredients for gemcitabine component:polyethylene glycol 8000, povidone K30, and urea.
Inactive ingredients for osmotic components:FD&C Blue No.1, polyethylene oxide 600,000, and urea.
Manufactured for:
Janssen Biotech, Inc.
Horsham, PA 19044, USA
U.S. License Number 1864
For patent information: www.janssenpatents.com
© Johnson & Johnson and its affiliates 2025
For more information, call 1-800-526-7736 or go to www.INLEXZO.com

This Patient Information has been approved by the U.S. Food and Drug Administration

Issued: 09/2025

INSTRUCTIONS FOR USE
INLEXZO™
[inn-lex-zo]
(gemcitabine intravesical system)
For Intravesical Administration Only

Intended Use

INLEXZO releases gemcitabine into bladder urine during the indwelling period. See INLEXZO Prescribing Information (PI) for additional details.

The contents of the Instructions for Use provide instructions for both the insertion and removal of INLEXZO. Ensure that the Instructions for Use are available and reviewed prior to insertion and removal of INLEXZO.

User

INLEXZO should be inserted and removed by a trained healthcare provider.

 | MRI Safety Information INLEXZOis MR Conditional. A patient with INLEXZOmay be safely scanned under the following conditions. Failure to follow these conditions may result in injury to the patient.
Parameter |  | Condition of Use/Information
Nominal Values of Static Magnetic Field (T) |  | 1.5-Tesla and 3.0-Tesla
Maximum Spatial Field Gradient (T/m and gauss/cm) |  | 50-T/m (5,000-gauss/cm)
Type of RF Excitation |  | Circularly Polarized (CP) (i.e., Quadrature Transmission)
Transmit RF Coil |  | Any transmit RF coil may be used.
Receive RF Coil |  | Any receive-only RF coil may be used
Maximum Whole Body Averaged SAR (W/kg) |  | 2-W/kg (Normal Operating Mode)
Limits on Scan Duration |  | Whole body averaged SAR of 2-W/kg for 60 minutes of continuous RF exposure (i.e., per pulse sequence or back-to-back sequences/series without breaks)
MR Image Artifact |  | The presence of INLEXZO produces an imaging artifact. Therefore, carefully select pulse sequence parameters if INLEXZO is located in the area of interest.

Precautions

INLEXZO is a hazardous drug. Follow applicable special handling and disposal procedures while handling INLEXZO and during the insertion and removal procedure. Dispose of the used urinary catheter and stylet, INLEXZO, and its packaging per facility procedures and per applicable federal, state, and local regulations.

Wear gloves, and take appropriate precautions, per local guidelines for handling hazardous drugs,to prevent skin or mucus membrane exposure while handling INLEXZO and during the insertion and removal procedure.

If contact with INLEXZO is suspected, immediately wash the skin thoroughly or rinse the mucosa with copious amounts of water.

Advise patients and caregivers to exercise caution when handling urine during indwelling period of approximately 3 weeks. See INLEXZO PI for details.

INLEXZO contains one single-dose 225 mg strength gemcitabine intravesical system consisting of a flexible bi-oval shaped tube containing an almost white to light pink-brown colored component at the center surrounded by off white to light blue osmotic components.

Important Information

Use aseptic technique during insertion and removal of INLEXZO.

Follow these instructions carefully, to avoid patient injury and ensure proper functioning.

Insertion

To ensure proper insertion of INLEXZO and to avoid damage to INLEXZO, use only the following:

- Water-based lubricant
- Urinary catheter and stylet (supplied)

Do notuse the urinary catheter and stylet for any other purpose. Do not re-sterilize/re-use the urinary catheter or stylet. Re-use of the urinary catheter and stylet can lead to its degradation, failure, and contamination, which can increase the risk of infection or transmission of blood borne pathogens to patients and users.

Do notuse any components that are damaged or have damaged packaging.

Check the expiration ('EXP') date before use.

Do notuse INLEXZO if expiration date has passed.

Removal

To ensure proper INLEXZO removal and to avoid damage to INLEXZO and/or cystoscope, use only the following:

- Non-cutting, grasping forceps
- Flexible or rigid cystoscope

Storage

Store in the original package at 20°C to 25°C(68°F to 77°F); with excursions permitted between 15°C to 30°C(59°F to 86°F) [see USP Controlled Room Temperature].

INLEXZO™
Intravesical System

Urinary Catheter and Stylet

Prepare components for INLEXZO insertion

1. Gather supplies

Included in the product carton:

- One sterile INLEXZO
- One sterile urinary catheter and one sterile stylet

Not included in the product carton:

- Multiple pairs of gloves
- Two 10 mL prefilled water-based lubricant syringes OR
- Two empty 10 mL syringes and water-based lubricant

2. Put on gloves

3. Prepare two syringes with sterile water-based lubricant

- Remove each sterile syringe prefilled with water-basedlubricant from its packaging and place each syringe on the sterile work surface using aseptic technique.
  OR
- Fill each of the two empty syringes with 2 mL to 3 mL of water-basedlubricant plus additional lubricant for urinary catheter tip lubrication.
- Place each lubricant syringe on a sterile work surface using aseptic technique.

- The lubricant is to be used to lubricate the tip of the urinary catheter and to facilitate the insertion of INLEXZO.

4. Open the INLEXZO foil pouch

1. Tear open the INLEXZO outer foil pouch at tear notch.
2. Remove the white INLEXZO inner pouch.

5. Examine the white component pouches for damage
Check the white INLEXZO pouch and white pouch containing the urinary catheter and stylet for damage (e.g., cuts, tears, punctures) that could compromise sterility of the components before opening.

Do not use if packaging is damaged.

Surfaces of the white INLEXZO pouch and the white component pouches are not sterile.

6. Open the white component pouches and transfer the contents onto a sterile work surface

1. Open the white INLEXZO pouch and transfer INLEXZO onto a sterile work surface.
2. Do not remove plastic sleeves from INLEXZO.
3. Open the white pouch containing the urinary catheter and stylet and transfer the contents onto a sterile work surface.

7. Put on sterile gloves

1. Ensure your patient is prepared for the procedure.
2. Put on sterile gloves.

8. Remove plastic sleeves
Remove the plastic sleeves from INLEXZO.

9. Inspect components
Inspect INLEXZO, the urinary catheter, and green stylet for damage.
Do notuse if the urinary catheter or green stylet are damaged or if the outer surface of INLEXZO is damaged.

Insert INLEXZO

1. Lubricate the urinary catheter
Lubricate tip of the urinary catheter. The urinary catheter should be free of INLEXZO and the stylet.

2. Insert the urinary catheter (without stylet)
Introduce the urinary catheter into the urethra by hand and advance until urine return. Do not empty the bladder.
Use depth markings to maintain coudé tip orientation and insertion depth position throughout the procedure.

Do not excessively force the urinary catheter into the bladder.

In case of resistance, careful assessment and standard procedural techniques can be performed, as appropriate, in order to safely advance the urinary catheter into the bladder.

If advancement is obstructed or cause cannot be determined or resolved, withdraw the urinary catheter to avoid patient injury or urinary catheter damage.

Do not re-use urinary catheter.

3. Inject lubricant from the first syringe into the urinary catheter
Inject 2 mL to 3 mL of lubricant from the first syringe into the end of the urinary catheter with the urinary catheter placed in the bladder.

4. Insert INLEXZO into the urinary catheter
Insert either end of INLEXZO into the urinary catheter and advance until fully inserted.

5. Inject lubricant from the second syringe into the urinary catheter
Inject 2 mL to 3 mL of lubricant from the second syringe into the urinary catheter to help advance INLEXZO further, with the urinary catheter placed in the bladder.

6. Insert stylet into the urinary catheter
Slowly insert the stylet into the urinary catheter until the stylet hub is flush with end of the urinary catheter. This ensures INLEXZO exits the urinary catheter and enters the bladder.

If INLEXZO cannot be advanced, remove the urinary catheter and stylet together as a single unit.

Ensure INLEXZO is also removed.

Do not attempt to re-use the removed INLEXZO.

Begin again by obtaining a new carton of INLEXZO including a new urinary catheter and stylet.

7. Remove the urinary catheter and stylet together as a single unit
Do notremove the urinary catheter and stylet individually.
INLEXZO should remain inside the bladder.
Retain Instructions for Use for the removal procedure.

Post-Insertion Instructions

1. Provide the completed MRI Safety Information Card to the patient
Remove the MRI Safety Information Card from the carton.
Complete the details and give it to the patient.
Advise the patient to carry the card and to show their current and future healthcare providers in case of need for MRI scans.

- INLEXZO contains a metal wire. The patient can safely undergo an MR exam only under very specific conditions (see MRI Safety Information).

2. Inform the patient and caregivers about the indwelling period

The indwelling period is approximately 3 weeks. See INLEXZO PI for additional information.

Inform the patient and caregivers that INLEXZO will remain in the bladder for the indwelling dosing period.

INLEXZO contains a hazardous drug. The patient and caregivers should be made aware of the need to exercise caution when handling urine during the indwelling period. See INLEXZO PI for additional information.

Removal of INLEXZO after the indwelling period

1. Lubricate the cystoscope
Use a water-based lubricant to lubricate the cystoscope.
2. Insert the cystoscope
Insert the cystoscope into the bladder to locate INLEXZO.

3. Grasp INLEXZO
Introduce non-cuttinggrasping forceps through the working channel of the cystoscope.

Do not use cutting forceps.

Grasp INLEXZO over tubing and metal wire.

Do not grasp on or near the ends of INLEXZO.

Grasping near the ends of INLEXZO could result in exposing the metal wire, potentially causing damage to surrounding tissue.

4. Remove INLEXZO
Remove the cystoscope and forceps out of the urethra togetherto remove INLEXZO under direct vision.
Do notremove INLEXZO through working channel of the cystoscope. Doing so may damage INLEXZO and/or the cystoscope.

5. Inspect INLEXZO

After removal, inspect INLEXZO to confirm it is intact and unbroken.

Manufactured for:
Janssen Biotech, Inc.
Horsham, PA 19044, USA.
U.S. License Number 1864

This Instructions for Use has been approved by the U.S. Food and Drug Administration.
Approved: 09/2025

For patent information:
www.janssenpatents.com
© Johnson & Johnson and its affiliates 2025

PRINCIPAL DISPLAY PANEL - 225 mg Intravesical System Box

NDC 57894-225-01

inlexzo™
(gemcitabine intravesical system)

225 mg

For lntravesical Use Only

Contents:

- One sterile single-dose gemcitabine intravesical system
- One sterile urinary catheter (17.5 Fr) and one sterile green stylet
- One MRI Safety Information Card
- One Instructions for Use
- Prescribing Information

WARNING: Hazardous Drug

MR Conditional

Rx only

Johnson
&Johnson

Each intravesical system contains 256.3 mg gemcitabine
hydrochloride (equivalent to 225 mg gemcitabine free base).

Gemcitabine hydrochloride mini-tablets inactive ingredients:
polyethylene glycol 8000 (8.0 mg), povidone K30 (13.4 mg), and urea (42.6 mg).

Osmotic mini-tablets inactive ingredients: FD&C Blue No. 1 (0.0042 mg),
polyethylene oxide 600,000 (72.0 mg), and urea (648.0 mg).

Not made with natural rubber latex.

Recommended Dosage: See Prescribing Information.

Store in the original carton at 20 °C to 25 °C (68 °F to 77 °F); with excursions permitted
between 15 °C to 30 °C (59 °F to 86 °F) [see USP Controlled Room Temperature].

For additional assistance or to share your feedback on lnlexzo™,
call 1-800-526-7736.

Active Ingredient Made in India.

Manufactured for:
Janssen Biotech, Inc.
Horsham, PA 19044, USA

Pat. www.janssenpatents.com

Scan here for additional
product information.
Standard Data Fees Apply.

OPEN HERE